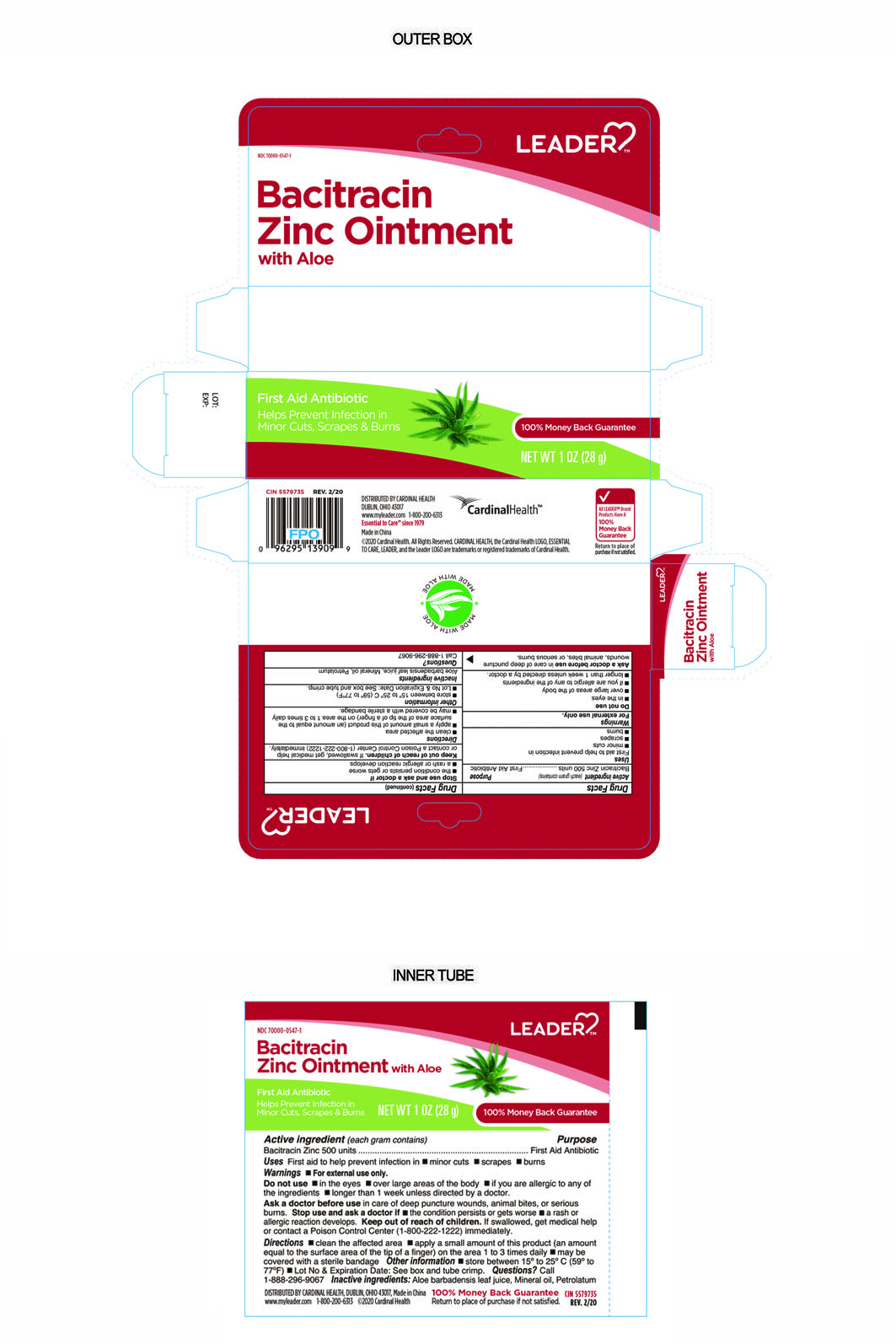 DRUG LABEL: Leader Bacitracin Zinc
NDC: 70000-0547 | Form: OINTMENT
Manufacturer: Cardinal Health 110 dba LEADER
Category: otc | Type: HUMAN OTC DRUG LABEL
Date: 20240102

ACTIVE INGREDIENTS: BACITRACIN ZINC 500 [USP'U]/1 g
INACTIVE INGREDIENTS: LIGHT MINERAL OIL; PETROLATUM; ALOE VERA LEAF

Bacitracin Zinc Ointment

Active Ingredient

Bacitracin Zinc 500 Units per gram

Purpose

First Aid Antibiotic

Uses

First Aid to help prevent infection in

- minor cuts
- scrapes
- burns

Warnings

For External Use Only.

Do Not Use

- in eyes
- over large areas of the body
- if you are allergic to any of the ingredients
- longer than 1 week unless directed by a doctor

Ask Doctor before Use

In care of deep puncture wounds, animal bites, or serious burns.

Stop Use and Ask Doctor if

- The condition persists or gets worse
- A rash or allergic reaction develops

Directions

- Clean the affected area
- Apply a small amount of this product (an amount equal to the surface area of the tip of a finger) on the area 1 to 3 times daily
- May be covered with a sterile bandage

Inactive Ingredients

Aloe barbadensis leaf juice, mineral oil, petrolatum

Questions

Call 1-800-200-6313

Keep out of reach of children

If swallowed, get medical help or contact a Poison Control Center (1-800-222-1222) immediately.

Other Information

Store Between 15° to 25°C (59° to 77°F)

Lot No. and Expiration Date: See box and tube crimp

Distributed By:

Cardinal Health

Dublin, Ohio 43017

www.myleader.com

1-800-200-6313

Essential to Care™ Since 1979

Made in China

©2020 Cardinal Health. All rights reserved. CARDINAL HEALTH, the Cardinal Health LOGO, ESSENTIAL TO CARE, LEADER, and the leader LOGO are trademarks or registered trademarks of Cardinal Health.